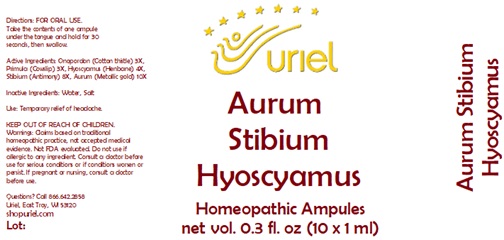 DRUG LABEL: Aurum Stibium Hyoscyamus
NDC: 48951-1205 | Form: LIQUID
Manufacturer: Uriel Pharmacy Inc.
Category: homeopathic | Type: HUMAN OTC DRUG LABEL
Date: 20231116

ACTIVE INGREDIENTS: ONOPORDUM ACANTHIUM FLOWER 3 [hp_X]/1 mL; PRIMULA VERIS FLOWER 3 [hp_X]/1 mL; HYOSCYAMUS NIGER LEAF 4 [hp_X]/1 mL; ANTIMONY 8 [hp_X]/1 mL; GOLD 10 [hp_X]/1 mL
INACTIVE INGREDIENTS: WATER; SODIUM CHLORIDE

Aurum Stibium Hyocyamus

INDICATIONS AND USAGE

Directions: FOR ORAL USE.

DOSAGE AND ADMINISTRATION

Take the contents of one ampule
under the tongue and hold for
30 seconds, then swallow.

ACTIVE INGREDIENT

Active Ingredients: Onopordon (Cotton thistle) 3X, Primula (Cowslip) 3X, Hyoscyamus (Henbane) 4X, Stibium (Antimony) 8X, Aurum (Metallic gold) 10X

Inactive Ingredients: Water, Salt

PURPOSE

Use: Temporary relief of headache.

KEEP OUT OF REACH OF CHILDREN.

KEEP OUT OF REACH OF CHILDREN.
Warnings: Claims based on traditional homeopathic practice, not accepted medical evidence. Not FDA evaluated. Do not use if allergic to any ingredient. Consult a doctor before use for serious conditions or if conditions worsen or persist. If pregnant or nursing, consult a doctor before use.

Questions? Call 866.642.2858
Uriel, East Troy, WI 53120
shopuriel.com